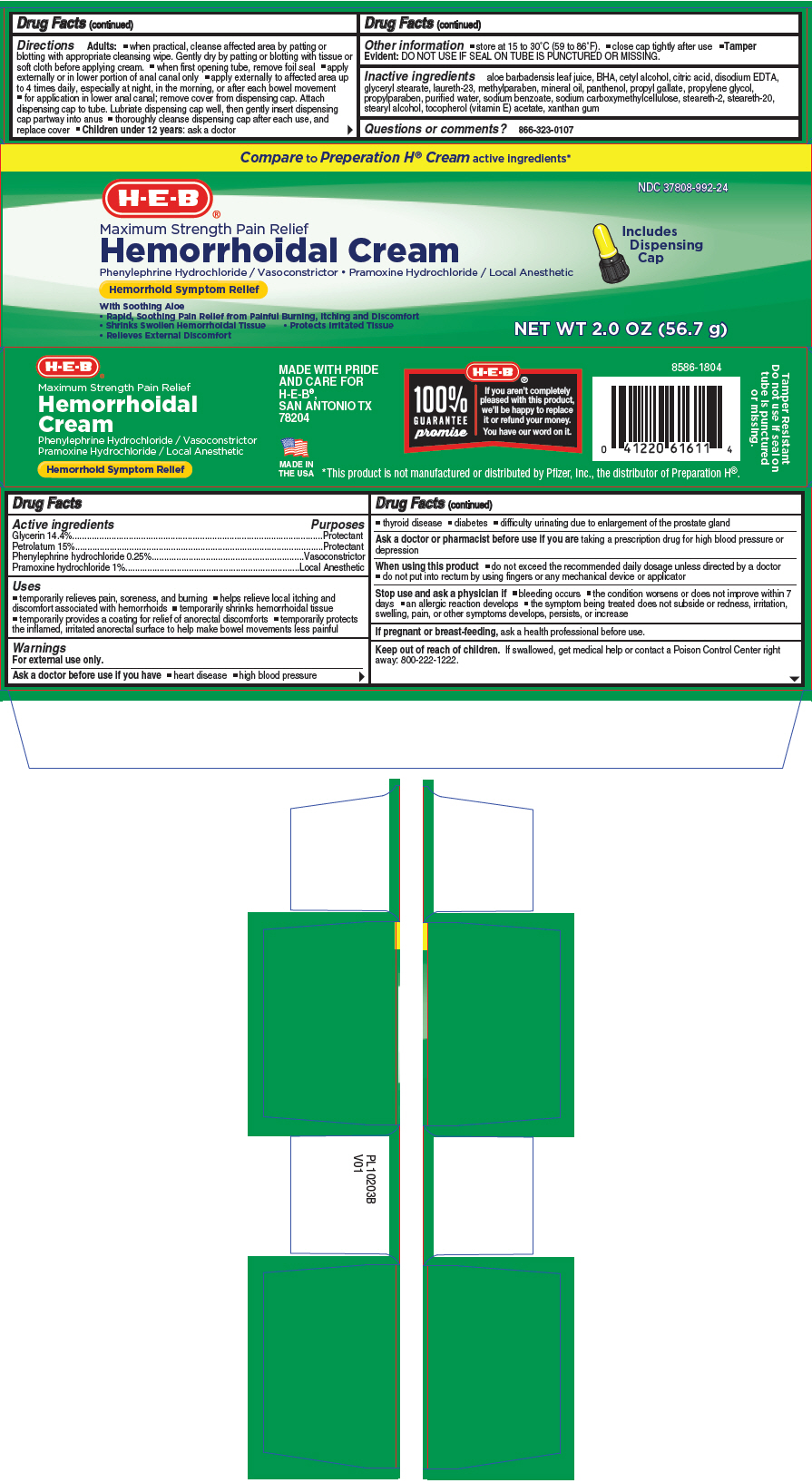 DRUG LABEL: HEB Maximum Strength Pain Relief Hemorrhoidal
NDC: 37808-992 | Form: CREAM
Manufacturer: HEB
Category: otc | Type: HUMAN OTC DRUG LABEL
Date: 20181022

ACTIVE INGREDIENTS: GLYCERIN 0.144 mg/2 g; PETROLATUM 0.15 mg/2 g; PHENYLEPHRINE HYDROCHLORIDE 0.0025 mg/2 g; PRAMOXINE HYDROCHLORIDE 0.1 mg/2 g
INACTIVE INGREDIENTS: ALOE VERA LEAF; BUTYLATED HYDROXYANISOLE; CETYL ALCOHOL; CITRIC ACID MONOHYDRATE; EDETATE DISODIUM; GLYCERYL MONOSTEARATE; LAURETH-23; METHYLPARABEN; MINERAL OIL; PANTHENOL; PROPYL GALLATE; PROPYLENE GLYCOL; PROPYLPARABEN; WATER; CARBOXYMETHYLCELLULOSE SODIUM, UNSPECIFIED FORM; STEARETH-2; STEARETH-20; STEARYL ALCOHOL; .ALPHA.-TOCOPHEROL ACETATE; XANTHAN GUM

HEB Maximum Strength Pain Relief Hemorrhoidal Cream

Drug Facts

ACTIVE INGREDIENT

PURPOSE

Active ingredients | Purposes
Glycerin 14.4% | Protectant
Petrolatum 15% | Protectant
Phenylephrine hydrochloride 0.25% | Vasoconstrictor
Pramoxine hydrochloride 1% | Local Anesthetic

Uses

- temporarily relieves pain, soreness, and burning
- helps relieve local itching and discomfort associated with hemorrhoids
- temporarily shrinks hemorrhoidal tissue
- temporarily provides a coating for relief of anorectal discomforts
- temporarily protects the inflamed, irritated anorectal surface to help make bowel movements less painful

Warnings

For external use only.

Ask a doctor before use if you have

- heart disease
- high blood pressure
- thyroid disease
- diabetes
- difficulty urinating due to enlargement of the prostate gland

Ask a doctor or pharmacist before use if you are taking a prescription drug for high blood pressure or depression

When using this product

- do not exceed the recommended daily dosage unless directed by a doctor
- do not put into rectum by using fingers or any mechanical device or applicator

Stop use and ask a physician if

- bleeding occurs
- the condition worsens or does not improve within 7 days
- an allergic reaction develops
- the symptom being treated does not subside or redness, irritation, swelling, pain, or other symptoms develops, persists, or increase

PREGNANCY OR BREAST FEEDING

If pregnant or breast-feeding, ask a health professional before use.

Keep out of reach of children. If swallowed, get medical help or contact a Poison Control Center right away: 800-222-1222.

Directions

Adults:

- when practical, cleanse affected area by patting or blotting with appropriate cleansing wipe. Gently dry by patting or blotting with tissue or soft cloth before applying cream.
- when first opening tube, remove foil seal
- apply externally or in lower portion of anal canal only
- apply externally to affected area up to 4 times daily, especially at night, in the morning, or after each bowel movement
- for application in lower anal canal; remove cover from dispensing cap. Attach dispensing cap to tube. Lubriate dispensing cap well, then gently insert dispensing cap partway into anus
- thoroughly cleanse dispensing cap after each use, and replace cover
- Children under 12 years: ask a doctor

Other information

- store at 15 to 30°C (59 to 86°F).
- close cap tightly after use
- Tamper Evident: DO NOT USE IF SEAL ON TUBE IS PUNCTURED OR MISSING.

Inactive ingredients

aloe barbadensis leaf juice, BHA, cetyl alcohol, citric acid, disodium EDTA, glyceryl stearate, laureth-23, methylparaben, mineral oil, panthenol, propyl gallate, propylene glycol, propylparaben, purified water, sodium benzoate, sodium carboxymethylcellulose, steareth-2, steareth-20, stearyl alcohol, tocopherol (vitamin E) acetate, xanthan gum

Questions or comments?

866-323-0107

PRINCIPAL DISPLAY PANEL - 56.7 g Tube Carton

Compare to Preperation H® Cream active ingredients*

NDC 37808-992-24

H-E-B®

Maximum Strength Pain Relief
Hemorrhoidal Cream
Phenylephrine Hydrochloride / Vasoconstrictor • Pramoxine Hydrochloride / Local Anesthetic

Hemorrhoid Symptom Relief

With Soothing Aloe
• Rapid, Soothing Pain Relief from Painful Burning, Itching and Discomfort
• Shrinks Swollen Hemorrhoidal Tissue • Protects Irritated Tissue
• Relieves External Discomfort

Includes
Dispensing
Cap

NET WT 2.0 OZ (56.7 g)